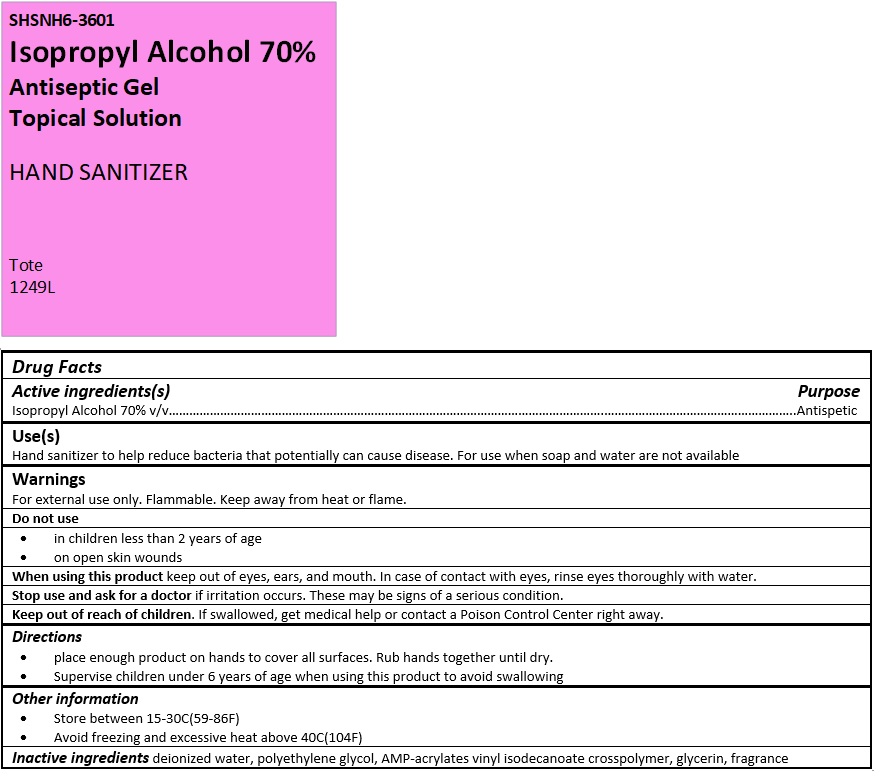 DRUG LABEL: SHSNH6-3601
NDC: 73870-516 | Form: GEL
Manufacturer: Shotwell Hydrogenics, LLC
Category: otc | Type: HUMAN OTC DRUG LABEL
Date: 20210409

ACTIVE INGREDIENTS: ISOPROPYL ALCOHOL 700 mL/1 L
INACTIVE INGREDIENTS: WATER; POLYETHYLENE GLYCOL, UNSPECIFIED; AMINOMETHYLPROPANOL; ACRYLATES/VINYL ISODECANOATE CROSSPOLYMER (10000 MPA.S NEUTRALIZED AT 0.5%); GLYCERIN

SHSNH6-3601 Antiseptic Gel HAND SANITIZER

Active ingredients(s)

Isopropyl Alcohol 70% v/v

Purpose

Antiseptic

Use(s)

Hand sanitizer to help reduce bacteria that potentially can cause disease. For use when soap and water are not available

Warnings

For external use only. Flammable. Keep away from heat or flame.

Do not use
• in children less than 2 years of age
• on open skin wounds
When using this product keep out of eyes, ears, and mouth. In case of contact with eyes, rinse eyes thoroughly with water.
Stop use and ask for a doctor if irritation occurs. These may be signs of a serious condition.

Keep out of reach of children. If swallowed, get medical help or contact a Poison Control Center right away.

Directions

• place enough product on hands to cover all surfaces. Rub hands together until dry.
• Supervise children under 6 years of age when using this product to avoid swallowing

Other information

• Store between 15-30C(59-86F)
• Avoid freezing and excessive heat above 40C(104F)

Inactive ingredients

deionized water, polyethylene glycol, AMP-acrylates vinyl isodecanoate crosspolymer, glycerin, fragrance

Topical Solution

HAND SANITIZER